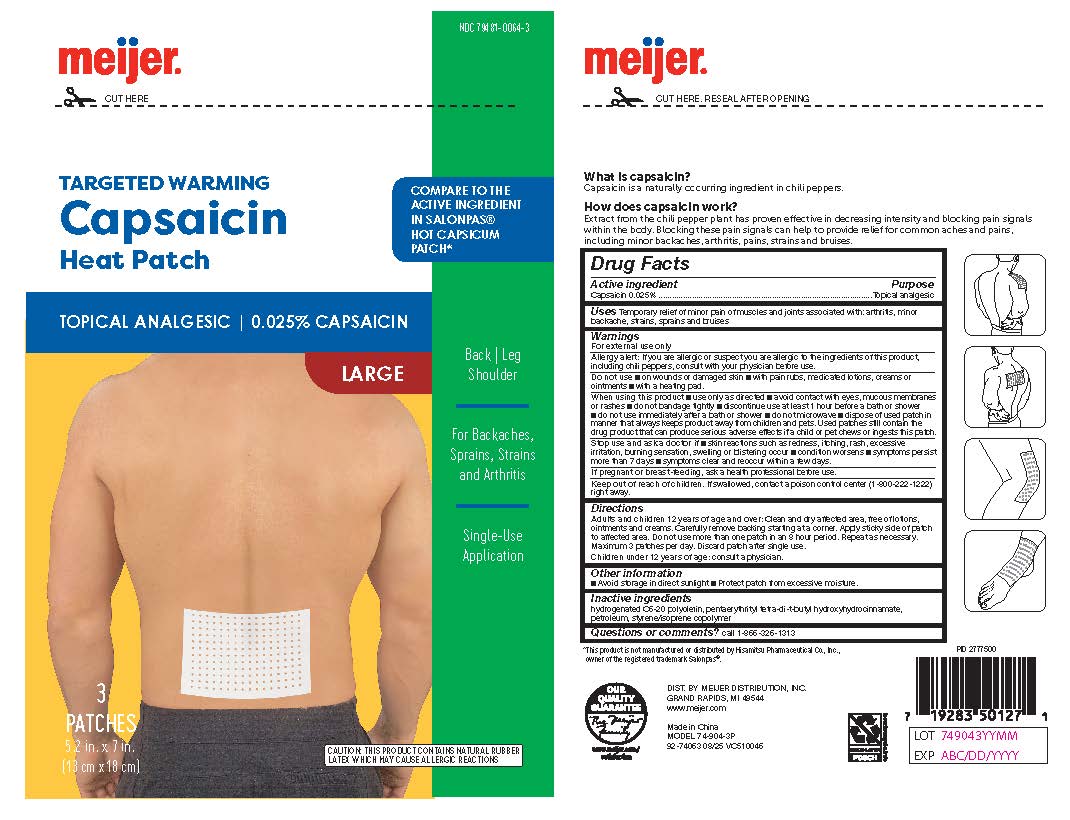 DRUG LABEL: Meijer Capsaicin Heat Patch
NDC: 79481-0064 | Form: PATCH
Manufacturer: Meijer Distribution
Category: otc | Type: HUMAN OTC DRUG LABEL
Date: 20250902

ACTIVE INGREDIENTS: CAPSAICIN 0.025 g/100 g
INACTIVE INGREDIENTS: HYDROGENATED POLYDECENE TYPE I; PENTAERYTHRITYL TETRA-DI-T-BUTYL HYDROXYHYDROCINNAMATE; LIQUID PETROLEUM; STYRENE/ACRYLAMIDE COPOLYMER (500000 MW)

Meijer Capsaicin Heat

Active Ingredient

Capsaicin 0.025%

Purpose

Topical analgesic

Uses

Temporary relief of minor pain of muscles and joints associated with: arthritis, minor
backache, strains, sprains and bruises

Do not use

■ on wounds or damaged skin ■ with pain rubs, medicated lotions, creams or
ointments ■ with a heating pad.

When using this product

■ use only as directed ■ avoid contact with eyes, mucous membranes
or rashes ■ do not bandage tightly ■ discontinue use at least 1 hour before a bath or shower
■ do not use immediately after a bath or shower ■ do not microwave ■ dispose of used patch in
manner that always keeps product away from children and pets. Used patches still contain the
drug product that can produce serious adverse effects if a child or pet chews or ingests this patch.

Stop use and ask a doctor if

■ skin reactions such as redness, itching, rash, excessive
irritation, burning sensation, swelling or blistering occur ■ condition worsens ■ symptoms persist
more than 7 days ■ symptoms clear and reoccur within a few days.

When using this product

■ use only as directed ■ avoid contact with eyes, mucous membranes
or rashes ■ do not bandage tightly ■ discontinue use at least 1 hour before a bath or shower
■ do not use immediately after a bath or shower ■ do not microwave ■ dispose of used patch in
manner that always keeps product away from children and pets. Used patches still contain the
drug product that can produce serious adverse effects if a child or pet chews or ingests this patch.

Keep out of reach of children.

If swallowed, contact a poison control center (1-800-222-1222) right away

Keep out of reach of children.

f swallowed, contact a poison control center (1-800-222-1222) right away.

Directions

Adults and children 12 years of age and over: Clean and dry affected area, free of lotions,
ointments and creams. Carefully remove backing starting at a corner. Apply sticky side of patch
to affected area. Do not use more than one patch in an 8 hour period. Repeat as necessary.
Maximum 3 patches per day. Discard patch after single use.
Children under 12 years of age: consult a physician.

Other Information

■ Avoid storage in direct sunlight ■ Protect patch from excessive moisture.

Inactive Ingredients

hydrogenated C6-20 polyolefin, pentaerythrityl tetra-di-t-butyl hydroxyhydrocinnamate, petroleum, styrene/isoprene copolymer

Questions or comments?

call 1-866-326-1313